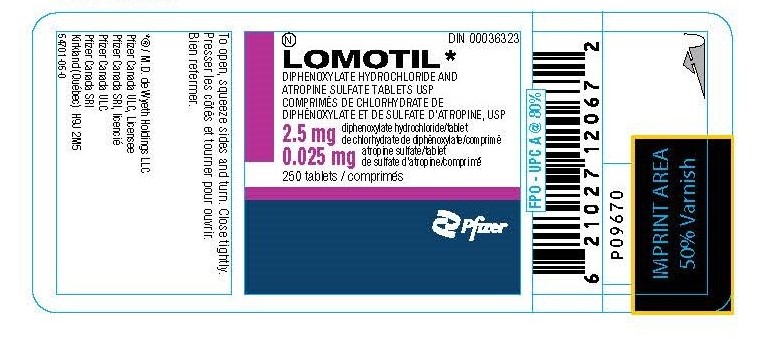 DRUG LABEL: LOMOTIL
NDC: 55466-783 | Form: TABLET
Manufacturer: Neolpharma, Inc.
Category: prescription | Type: HUMAN PRESCRIPTION DRUG LABEL
Date: 20251110
DEA Schedule: CV

ACTIVE INGREDIENTS: DIPHENOXYLATE HYDROCHLORIDE 2.5 mg/1 1; ATROPINE SULFATE 0.025 mg/1 1
INACTIVE INGREDIENTS: SORBITOL; STARCH, CORN; TALC; LIGHT MINERAL OIL; MAGNESIUM STEARATE; SUCROSE; ACACIA

LOMOTIL 2.5mg/0.025mg DIPHENOXYLATE HYDROCHLORIDE AND ATROPINE SULFATE TABLETS USP
Neolpharma as CMO